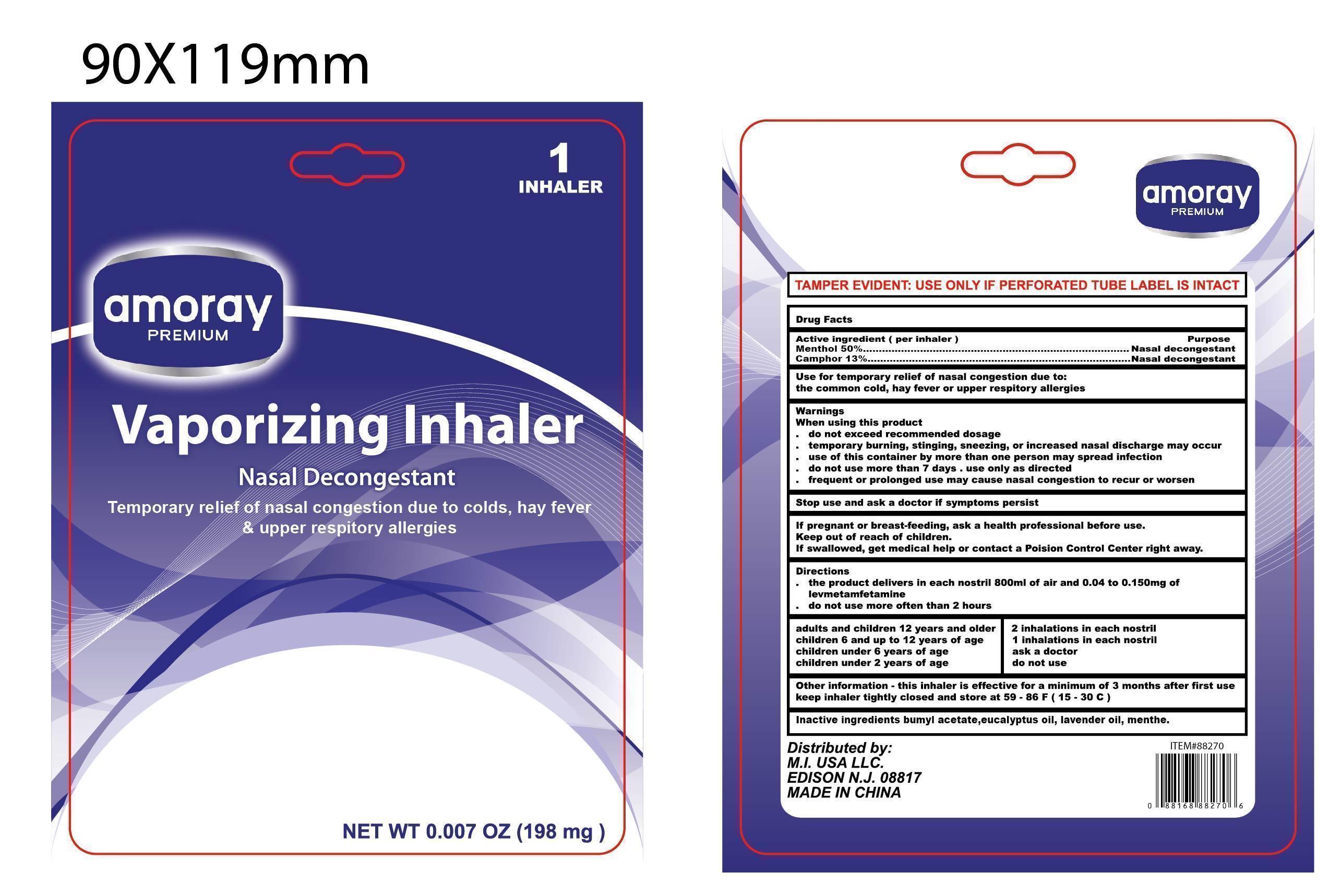 DRUG LABEL: amoray premium Vaporizing Inhaler
NDC: 40104-800 | Form: LIQUID
Manufacturer: Ningbo Pulisi Daily Chemical Products Co.,Ltd.
Category: otc | Type: HUMAN OTC DRUG LABEL
Date: 20160331

ACTIVE INGREDIENTS: CAMPHOR (NATURAL) 13 mg/1 1
INACTIVE INGREDIENTS: MENTHOL 50 mg/1 1; EUCALYPTUS OIL; BORNYL ACETATE; LAVENDER OIL

Active Ingredients

Menthol 50% ................... Nasal Decongestant

camphor 13% .................. Nasal Decongestant

Purpose

Nasal Decongestant

INDICATIONS:

USE FOR TEMPORARY RELIEF OF NASAL CONGESTION DUE TO:

The COMMON COLD, HAY FEVER OR UPPER RESPIRATORY ALLERGIES.

Warnings:

When using this product

- DO NOT EXCEED RECOMMENDED DOSAGE.
- Temporary BURNING, STINGING, SNEEZING, OR AN INCREASED IN NASAL DISCHARGE may occur.
- THE USE OF THIS CONTAINER BY MORE THAN ONE PERSON MAY SPREAD INFECTION.
- DO NOT USE THIS PRODUCT FOR MORE THAN 7 DAY. USE ONLY AS DISRECTED.
- FREQUENT OR PROLONGED USE MAY CAUSE NASAL CONGESTION TO RECUR OR WORSEN.

KEEP OUT OF REACH OF CHILDREN

KEEP THIS AND ALL DRUGS OUT OF THE REACH OF CHILDREN. if swallowed, get medical help or contact a Poision Control Center right away.

DIRECTIONS:

- THE PRODUCT DELIVERS IN EACH 800ML OF AIR 0.04 TO 0.150 MG OF LEVMETAMFETAMINE.
- Do not use more often than 2 hours.

ADULTS AND CHILDREN 12 YEARS OF AGE AND OVER: 2 INHALATIONS IN EACH NOSTRIL.

CHILDREN 6 TO 12 YEARS OF AGE (WITH ADULT SUPERVISION): 1 INHALATION IN EACH NOSTRIL.

CHILDREN UNDER 6 YEARS OF AGE: CONSULT A DOCTOR.

Childre nuder 2 years of age: DO NOT USE.

Inactive Ingredients:

BUMYL ACETATE, EUCALYTUS OIL, LAVENDER OIL, MENTHE

OTHER SAFETY INFORMATION

THIS INHALER IS EFFECTIVE FOR A MINIMUM OF 3 MONTHS AFTER FIRST USE. KEEP INHALER TIGHTLY CLOSED AND STORE AT 59-86 F (15-30 C)